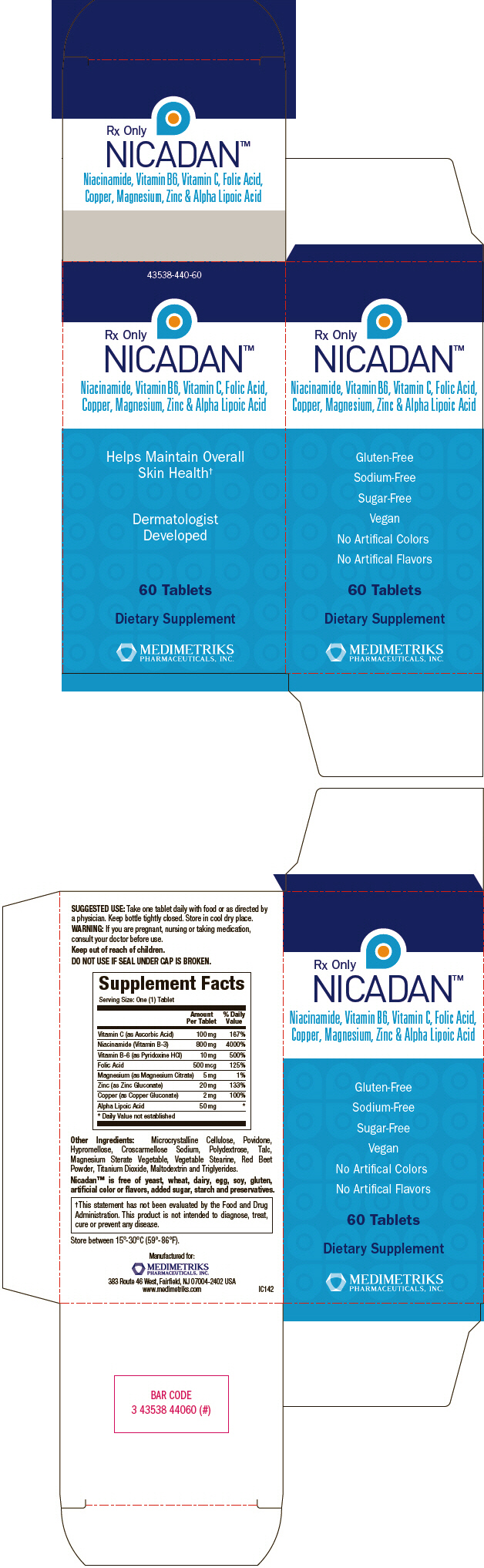 DRUG LABEL: Nicadan
NDC: 43538-440 | Form: TABLET, FILM COATED
Manufacturer: Medimetriks Pharmaceuticals, Inc.
Category: other | Type: DIETARY SUPPLEMENT
Date: 20140228

ACTIVE INGREDIENTS: Ascorbic Acid 100 mg/1 1; Niacinamide 800 mg/1 1; pyridoxine hydrochloride 10 mg/1 1; folic acid 500 ug/1 1; magnesium citrate 5 mg/1 1; zinc gluconate 20 mg/1 1; copper gluconate 20 mg/1 1; .alpha.-lipoic acid 50 mg/1 1
INACTIVE INGREDIENTS: cellulose, microcrystalline; povidones; hypromelloses; croscarmellose sodium; polydextrose; talc; titanium dioxide; maltodextrin

NICADAN™

HEALTH CLAIM

Rx Only

Niacinamide, Vitamin B6, Vitamin C, Folic Acid,
Copper, Magnesium, Zinc & Alpha Lipoic Acid

DESCRIPTION

Nicadan™ tablets are a specially formulated dietary supplement containing natural ingredients with anti-inflammatory properties. Each pink-coated tablet is oval shaped, scored and embossed with "MM". Nicadan™ is for oral administration only.

Nicadan™ should be administered under the supervision of a licensed medical practitioner.

INGREDIENTS

Each tablet of Nicadan™ contains:

Vitamin C (as Ascorbic Acid) | 100 mg
Niacinamide (Vitamin B-3) | 800 mg
Vitamin B-6 (as Pyridoxine HCI) | 10 mg
Folic Acid | 500 mcg
Magnesium (as Magnesium Citrate) | 5 mg
Zinc (as Zinc Gluconate) | 20 mg
Copper (as Copper Gluconate) | 2 mg
Alpha Lipoic Acid | 50 mg

Other Ingredients: Microcrystalline cellulose, Povidone, Hypromellose, Croscarmellose Sodium, Polydextrose, Talc, Magnesium Sterate Vegetable, Vegetable Stearine, Red Beet Powder, Titanium Dioxide, Maltodextrin and Triglycerides.

Nicadan™ is free of yeast, wheat, dairy, egg, soy, gluten, artificial color or flavors, added sugar, starch and preservatives.

USES

As a dietary supplement, Nicadan™ tablets are beneficial in maintaining overall skin health, especially in patients with inflammatory skin conditions. [This statement has not been evaluated by the Food and Drug Administration. This product is not intended to diagnose, treat, cure or prevent any disease.]

WARNINGS

If you are pregnant, nursing or taking medication, consult your doctor before use.

CONTRAINDICATIONS

Use of Nicadan™ is contraindicated in patients who are hypersensitive to any ingredient in this tablet.

PRECAUTIONS

There have been reports of GI upset, nausea, vomiting, heartburn, diarrhea, dizziness, drowsiness or headache with large doses of niacinamide. Rarely, niacinamide in doses of 3 grams/day or more has been associated with elevated liver function tests. There are case reports in the literature indicating that niacinamide may reduce the hepatic metabolism of primidone and carbamazepine. Individuals taking these medications should consult their physician. Individuals taking antidiabetes medications should have their blood glucose levels monitored.

Allergic sensitization has been reported rarely following oral administration of folic acid. Folic acid above 1 mg daily may obscure pernicious anemia in that hematologic remission may occur while neurological manifestations remain progressive.

DOSAGE AND ADMINISTRATION

Take one tablet daily with food or as directled by a physician. Nicadan™ tablets are scored, so they may be broken in half if required.

HOW SUPPLIED

Nicadan™ is available in a bottle containing 60 tablets. 43538-440-60

Store at 15°C to 30°C (59°F to 86°F). Keep bottle tightly closed. Store in cool dry place.

SAFE HANDLING WARNING

KEEP THIS AND ALL MEDICATIONS OUT OF THE REACH OF CHILDREN.

You may report side effects by calling 1-973-882-7512.

Manufactured for:

MEDIMETRIKS
PHARMACEUTICALS, INC.

383 Route 46 West, Fairfield, NJ 07004-2402 USA

www.medimetriks.com

Iss: 2/2014

IP038

PRINCIPAL DISPLAY PANEL - 60 Tablet Bottle Carton

43538-440-60

Rx Only
NICADAN™

Niacinamide, Vitamin B6, Vitamin C, Folic Acid,
Copper, Magnesium, Zinc & Alpha Lipoic Acid

Helps Maintain Overall
Skin Health†

Dermatologist
Developed

60 Tablets

Dietary Supplement

MEDIMETRIKS
PHARMACEUTICALS, INC.